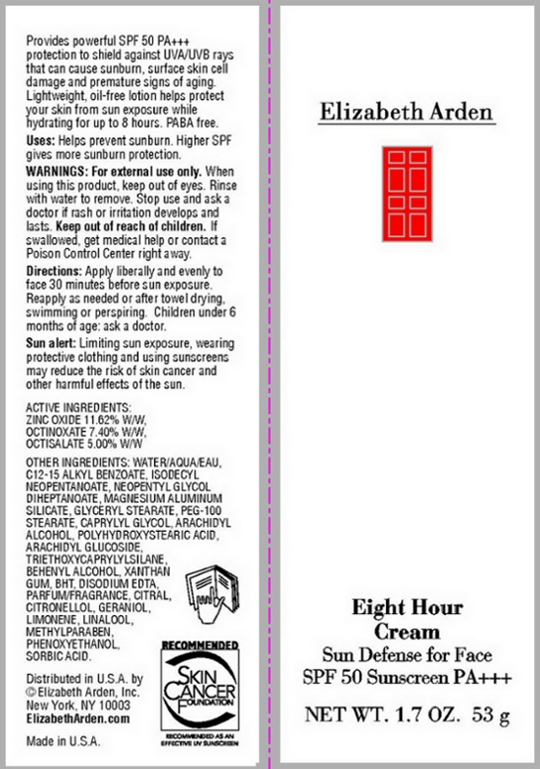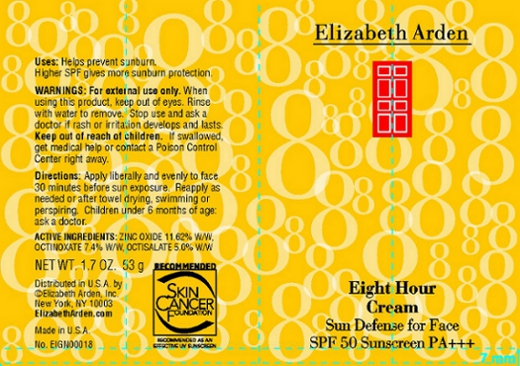 DRUG LABEL: Eight Hour Cream Sun Defense for Face SPF 50 Sunscreen
NDC: 67938-1094 | Form: LOTION
Manufacturer: Elizabeth Arden, Inc
Category: otc | Type: HUMAN OTC DRUG LABEL
Date: 20110114

ACTIVE INGREDIENTS: ZINC OXIDE 6.159 g/53 g; OCTINOXATE 3.922 g/53 g; OCTISALATE 2.65 g/53 g
INACTIVE INGREDIENTS: WATER; ALKYL (C12-15) BENZOATE; ISODECYL NEOPENTANOATE; NEOPENTYL GLYCOL DIHEPTANOATE; MAGNESIUM ALUMINUM SILICATE; GLYCERYL MONOSTEARATE; PEG-100 STEARATE; ARACHIDYL ALCOHOL; PHENOXYETHANOL; CAPRYLYL GLYCOL; DOCOSANOL; TRIETHOXYCAPRYLYLSILANE; XANTHAN GUM; EDETATE DISODIUM; METHYLPARABEN; ARACHIDYL GLUCOSIDE; SORBIC ACID; BUTYLATED HYDROXYTOLUENE

BC1094

DESCRIPTION

Provides powerful SPF 50 PA+++ protection to shield against UVA/UVB rays that can cause sunburn, surface skin cell damage and premature signs of aging. Lightweight, oil-free lotion helps protect your skin from sun exposure while hydrating for up to 8 hours. PABA free.

Uses: Helps prevent sunburn. Higher SPF gives more sunburn protection.

Sun Alert: Limiting sun exposure, wearing protective clothing and using sunscreens may reduce the risk of skin cancer and other harmful effects of the sun.

INDICATIONS AND USAGE

Directions: Apply liberally and evenly to face 30 minutes before sun exposure. Reapply as needed or after towel drying, swimming, or perspiring. Children under 6 months of age: ask a doctor.

WARNINGS

Warnings: For external use only. When using this product, keep out of eyes. Rinse with water to remove. Stop use and ask a doctor is rash or irritation develops and lasts. Keep out of reach of children. If swallowed, get medical help or contact a Poison Control Center right away.

OTC - ACTIVE INGREDIENT

Active Ingredients: Zinc Oxide 11.62% w/w, Octinoxate 7.40% w/w, Octisalate 5.00% w/w.

INACTIVE INGREDIENT

Water/Aqua/Eau, C12-25 Alkyl Benzoate, Isodecyl Neopentanoate, Neopentyl Glycol Diheptanoate, Magnesium Aluminum Silicate, Glyceryl Stearate, PEG-100 Stearate, Caprlyl Glycol, Arachidyl Alcohol, Polyhydroxystearic Acid, Arachidyl Glucoside, Triethoxycaprylylsilane, Behenyl Alcohol, Xanthan Gum, BHT, Disodium EDTA, Parfum/Fragrance, Citral, Citronellol, Geraniol, Limonene, Linalool, Methylparaben, Phenoxyethanol, Sorbic Acid.

DOSAGE & ADMINISTRATION

Apply liberally and evenly to face.

OTC - KEEP OUT OF REACH OF CHILDREN

Keep out of reach of children.

OTC - PURPOSE

Helps prevent sunburn. Higher SPF gives more sunburn protection.

OTC - WHEN USING

Keep out of eyes.